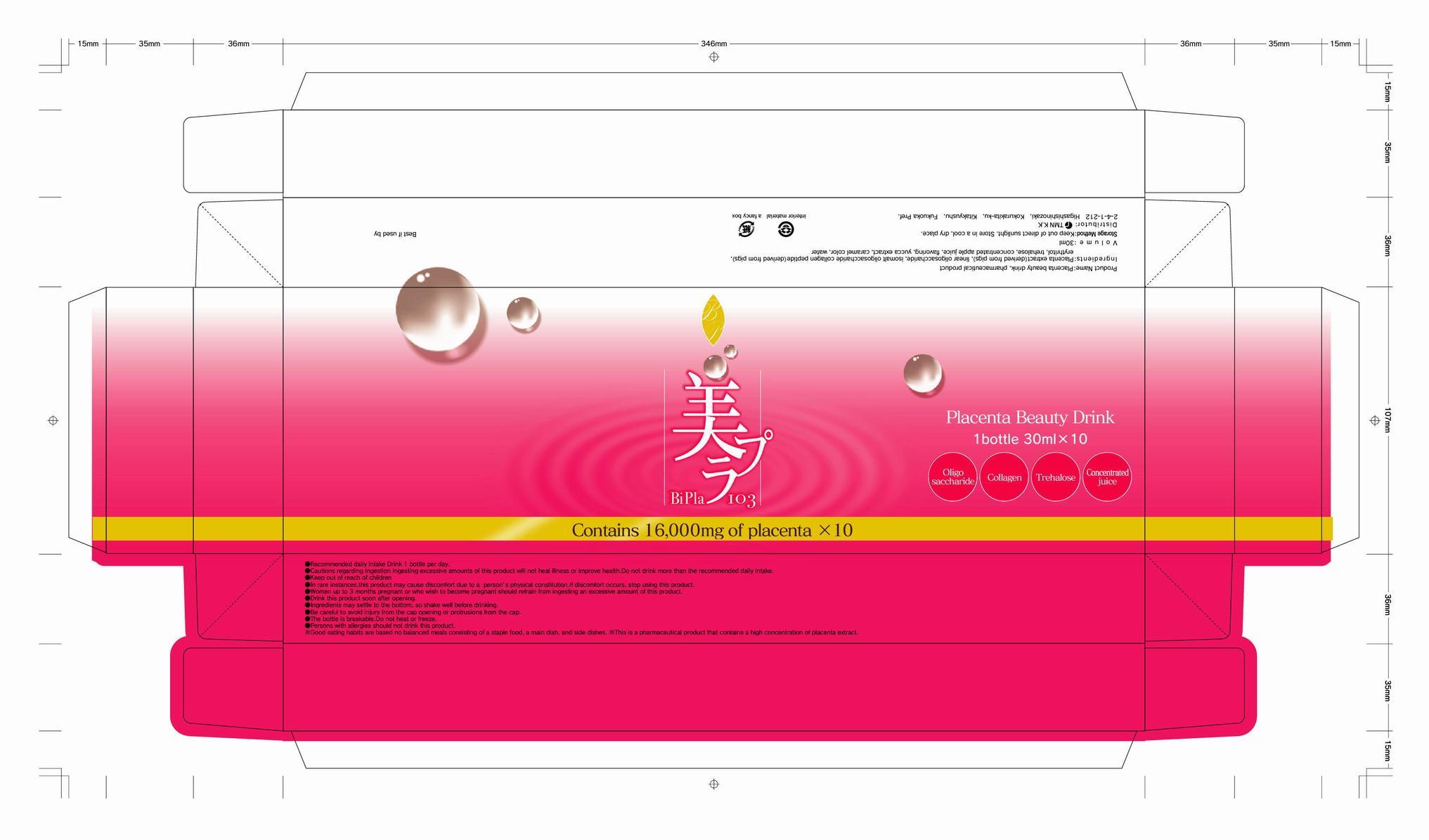 DRUG LABEL: BiPla
                
NDC: 52964-1001 | Form: LIQUID
Manufacturer: TMN K.K.
Category: otc | Type: HUMAN OTC DRUG LABEL
Date: 20120802

ACTIVE INGREDIENTS: SUS SCROFA PLACENTA 16000 mg/30 mL
INACTIVE INGREDIENTS: ERYTHRITOL; TREHALOSE; APPLE JUICE; MALIC ACID; CARAMEL

Drug Facts

active ingredient: placenta extract

inactive ingredient: erythritol, trehalose, apple juice, DL-malic acid, straight chain oligo saccharide, iso malto oligo saccharide, collagen peptide, yucca form, caramel pigment, spice

PURPOSE

for skin beauty

keep out of reach of the children

INDICATIONS AND USAGE

recommended daily intake: drink 1 bottle per day

WARNINGS

- persons with allergies should not drink this product
- the bottle is breakable. do not heat or freeze
- women up to 3 months pregnant or who wish to become pregnant should refrain from ingesting an excessive amount of this product

DOSAGE AND ADMINISTRATION

- ingredients may settle to the bottom, so shake well before drinking